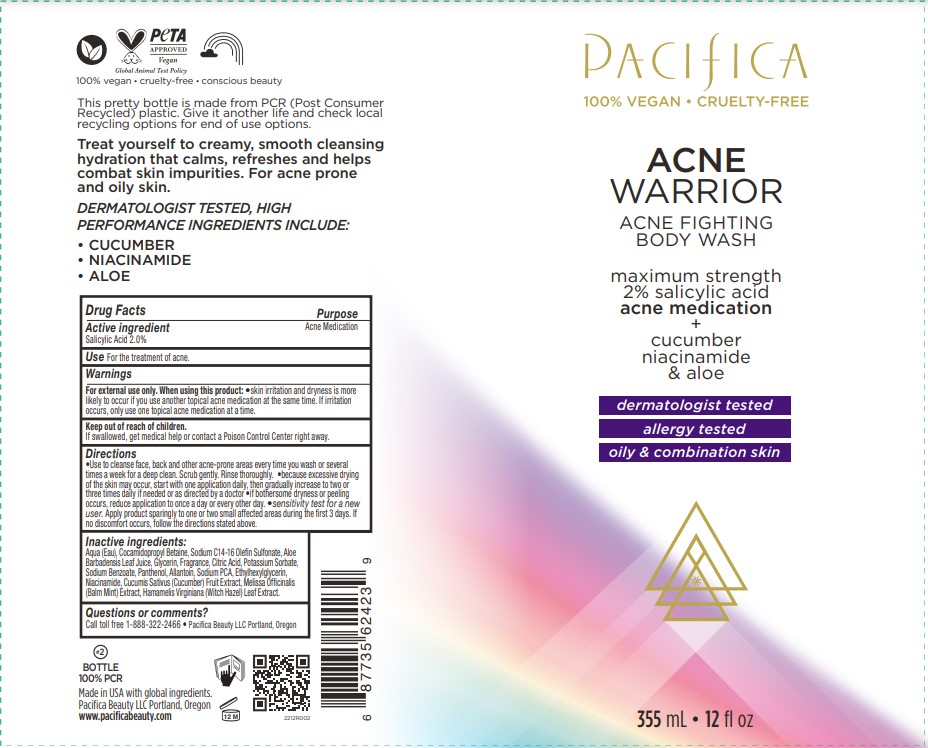 DRUG LABEL: Acne Warrior Body Wash
NDC: 61197-123 | Form: LIQUID
Manufacturer: Pacifica Beauty, LLC
Category: otc | Type: HUMAN OTC DRUG LABEL
Date: 20250103

ACTIVE INGREDIENTS: SALICYLIC ACID 2 g/100 mL
INACTIVE INGREDIENTS: CITRIC ACID MONOHYDRATE; ALLANTOIN; POTASSIUM SORBATE; CUCUMBER FRUIT OIL; WATER; SODIUM BENZOATE; ETHYLHEXYLGLYCERIN; ALOE VERA LEAF; COCAMIDOPROPYL BETAINE; SODIUM C14-16 OLEFIN SULFONATE; GLYCERIN; MELISSA OFFICINALIS LEAF; PANTHENOL; SODIUM PYRROLIDONE CARBOXYLATE; NIACINAMIDE; HAMAMELIS VIRGINIANA LEAF

Acne Warrior Body Wash

Active ingredient Purpose

Salicylic Acid 2.0% Acne Medication

Use

For the treatment of acne.

Warnings

For external use only. When using this product: skin irritation and dryness is more likely to occur if you use another topical acne medication at the same time. If irritation occurs, only use one topical acne medication at a time.

When using this product: skin irritation and dryness is more likely to occur if you use another topical acne medication at the same time. If irritation occurs, only use one topical acne medication at a time.

Keep out of reach of children. If swallowed, get medical help or contact a Poison Control Center right away.

Directions

Use to cleanse face, back and other acne-prone areas every time you wash or several times a week for a deep clean. Scrub gently. Rinse thoroughly. Because excessive drying of the skin may occur, start with one application daily, then gradually increase to two or three times daily if needed or as directed by a doctor If bothersome dryness or peeling occurs, reduce application to once a day or every other day. Sensitivity test for a new user. Apply product sparingly to one or two small affected areas during the first 3 days. If no discomfort occurs, follow the directions stated above.

Inactive ingredients:

Aqua (Eau), Cocamidopropyl Betaine, Sodium C14-16 Olefin Sulfonate, Aloe Barbadensis Leaf Juice, Glycerin, Fragrance, Citric Acid, Potassium Sorbate, Sodium Benzoate, Panthenol, Allantoin, Sodium PCA, Ethylhexylglycerin, Niacinamide, Cucumis Sativus (Cucumber) Fruit Extract, Melissa Officinalis (Balm Mint) Extract, Hamamelis Virginiana (Witch Hazel) Leaf Extract.

Questions or comments?

Call toll free 1-888-322-2466 Pacifica Beauty LLC Portland, Oregon